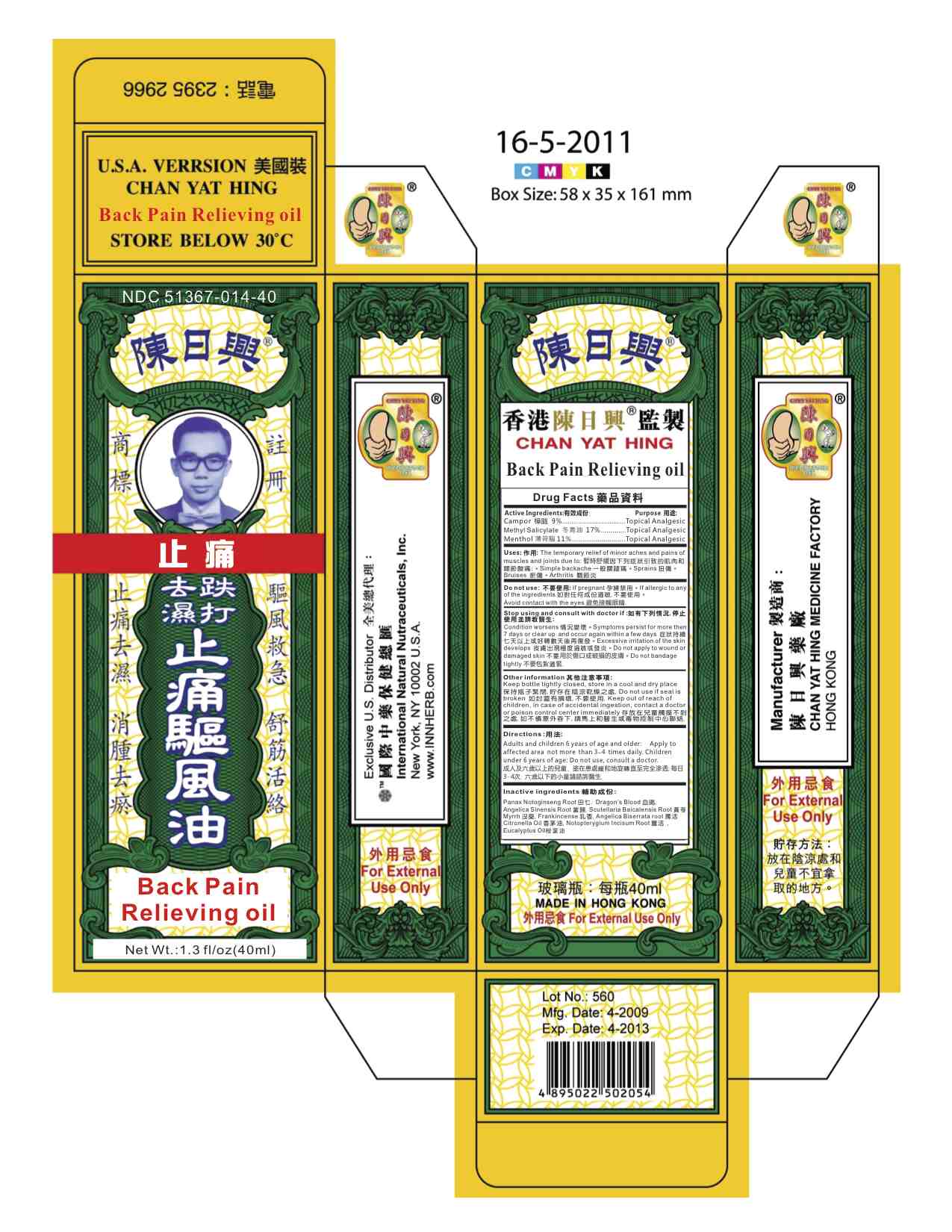 DRUG LABEL: Back Pain Relieving Oil
NDC: 51367-014 | Form: OIL
Manufacturer: International Nature Nutraceuticals
Category: otc | Type: HUMAN OTC DRUG LABEL
Date: 20131020

ACTIVE INGREDIENTS: CAMPHOR (NATURAL) 3.49 g/1 1; METHYL SALICYLATE 7.98 g/1 1; MENTHOL 3.92 g/1 1
INACTIVE INGREDIENTS: PANAX NOTOGINSENG ROOT; DRAGON'S BLOOD; ANGELICA SINENSIS ROOT; SCUTELLARIA BAICALENSIS ROOT; MYRRH; FRANKINCENSE; ANGELICA BISERRATA ROOT; CITRONELLA OIL; NOTOPTERYGIUM INCISUM ROOT; EUCALYPTUS OIL

Drug Facts

Active Ingredients:

Camphor- 9%

Methyl Salicylate- 17%

Menthol 11%

Uses:

The temporary relief of minor aches and pains of

muscles and joints due to: 暫時舒緩因下列症狀引致的肌肉和

關節酸痛:。Simple backache 一般腰腿痛。Sprains 扭傷。

Bruises 瘀傷。Arthritis 關節炎

Warning:

For external use only

Do Not Use:

If pregnant 孕婦禁用。If allergic to any

of the ingredients 如對任何成份過敏,不要使用。

Avoid contact with the eyes 避免接觸眼睛.

Stop use and consult a doctor if:

Condition worsens 情況變壞。Symptoms persist for more then

7 days or clear up and occur again within a few days 症狀持續

七天以上或好轉數天後再復發。Excessive irritation of the skin

develops 皮膚出現極度過敏或發炎。Do not apply to wound or

damaged skin 不要用於傷口或破損的皮膚。Do not bandage

tightly 不要包紮過緊.

Keep out of reach of children.

In case of accidental ingestion, contact a doctor

or poison control center immediately 存放在兒童觸摸不到

之處,如不慎意外吞下,請馬上和醫生或毒物控制中心聯絡.

Directions:

Adults and children 6 years of age and older: Apply to

affected area not more than 3~4 times daily. Children

under 6 years of age: Do not use, consult a doctor.

成人及六歲以上的兒童, 塗在患處緩和地旋轉直至完全滲透,每日

3-4次. 六歲以下的小童請諮詢醫生.

Other Information:

Keep bottle tightly closed, store in a cool and dry place

保持瓶子緊閉,貯存在陰涼乾燥之處.Do not use if seal is

broken 如封蓋有損壞,不要使用.Keep

Inactive Ingredients:

Panax Notoginseng Root 田七.

Angelica Sinensis Root 當歸.Scutellaria Baicalensis Root 黃苓

Myrrh 沒藥,Frankincense 乳香,

Citronella Oil 香茅油,Notopterygium Incisum Root 薑活

Eucalyptus Oil桉葉油

Dragon’s Blood 血竭,

Angelica Biserrata root 獨活